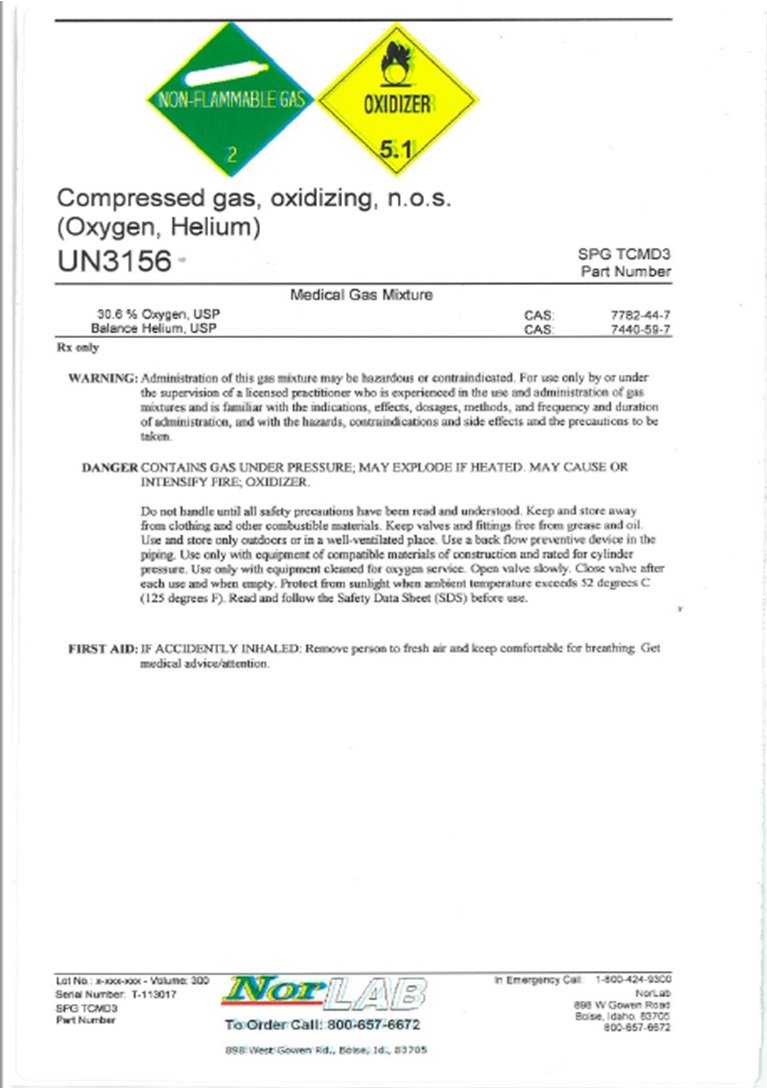 DRUG LABEL: COMPRESSED Gas OXIDIZING, N.O.S.
NDC: 42602-008 | Form: GAS
Manufacturer: Norco, Inc.
Category: prescription | Type: HUMAN PRESCRIPTION DRUG LABEL
Date: 20251215

ACTIVE INGREDIENTS: OXYGEN 30 L/100 L; HELIUM 70 L/100 L

COMPRESSED GAS OXIDIZING, N.O.S. LABEL 30% OXYGEN USP BALANCE HELIUM, USP

NON-FLAMMABLE GAS 2 OXIDIZER 5.1
Compressed gas, oxidizing, n.o.s.
(Oxygen, Helium)
UN 3156 SPG TCMD3

Part Number

___________________________________________________________________________

Medical Gas Mixture
30% Oxygen, USP CAS: 7782-44-7
Balance Heliun, USP CAS: 7440-59-7

___________________________________________________________________________

Rx only

WARNING:Administration of this gas mixture may be hazardous or contraindicated. For use only by or under
the supervision of a licensed practitioner who is experienced in the use and administration of gas
mixtures and is familiar with the indications, effects, dosages, methods, and frequency and duration
of administration, and with the hazards, contraindications and side effects and the precautions to be
taken.

DANGER:CONTAINS GAS UNDER PRESSURE; MAY EXPLODE IF HEATED. MAY CAUSE OR
INTENSIFY FIRE; OXIDIZER.

Do not handle until all safety precautions have been read and understood. Keep and store away
from clothing and other combustible materials. Keep valves and fittings free from grease and oil.
Use and store only outdoors or in a well-ventilated place. Use a back flow preventive device in the
piping. Use only with equipment of compatible materials of construction and rated for cylinder
pressure. Use only with equipment cleaned for oxygen service. Open valve slowly. Close valve after
each use and when empty. Protect from sunlight when ambient temperature exceeds 52 degrees C
(125 degrees F). Read and follow the Safety Data Sheet (SDS) before use.

FIRST AID:IF ACCIDENTALLY INHALED; Remove to fresh air and keep comfortable for breathing. Get
medical advice/attention.

___________________________________________________________________________________________________
Lot No: x-xxx-xxx – Volume 300 NorLAB In Emergency Call: 1-800-424-9300
Serial Number: T-113017 To Order Call: 800-657-6672 NorLab
SPG TCMD3 Part Numbe 898 W. Gowen Rd., Boise, ID 83507 898 W. Gowen Road

Boise, ID 83507

800-657-6572

res